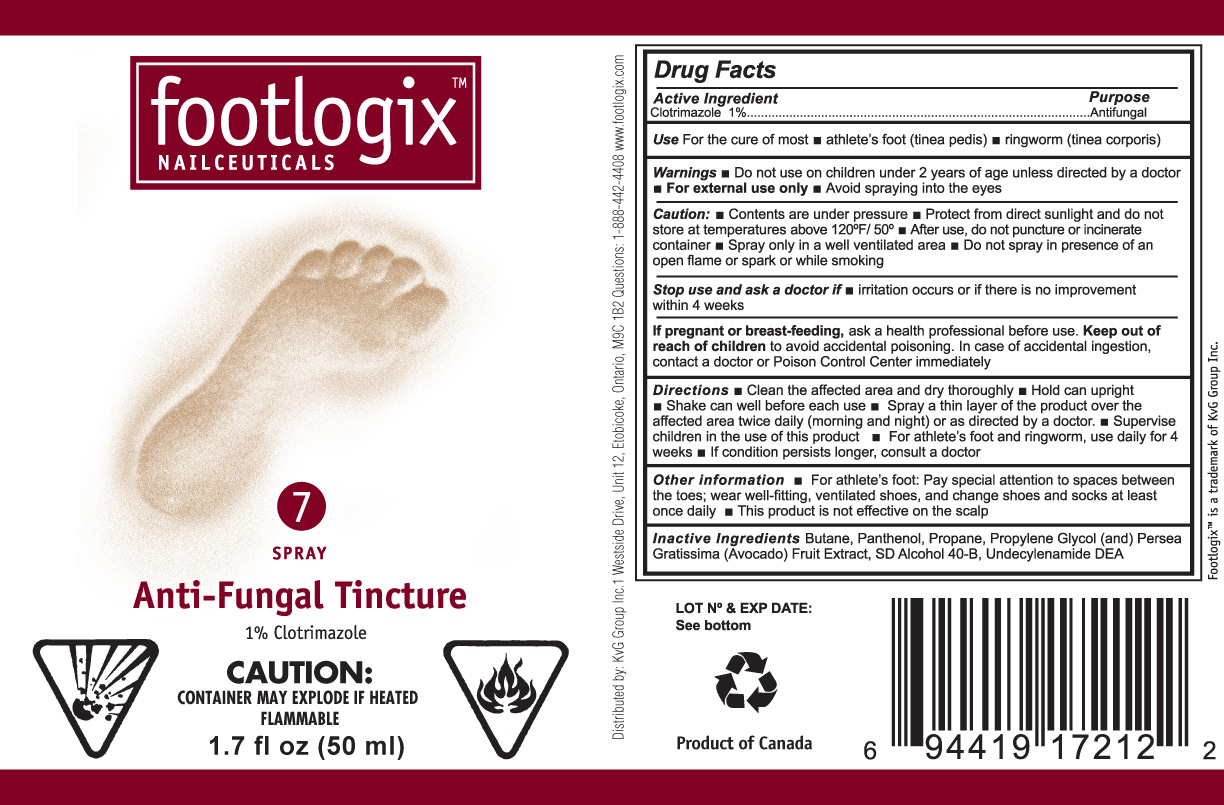 DRUG LABEL: footlogix 
NDC: 42479-212 | Form: AEROSOL, SPRAY
Manufacturer: KVG Group Inc 
Category: otc | Type: HUMAN OTC DRUG LABEL
Date: 20100819

ACTIVE INGREDIENTS: CLOTRIMAZOLE 1 mL/100 mL
INACTIVE INGREDIENTS: BUTANE; PANTHENOL; PROPANE; PROPYLENE GLYCOL; AVOCADO

Drug Facts

Active Ingredient
Clotrimazole 1%

Purpose
Antifungal

Use

- For the cure of most athlete’s foot (tinea pedis)
- ringworm (tinea corporis)

Warnings

- For external use only
- Do not use on children under 2 years of age unless directed by a doctor
- For external use only
- Avoid spraying into the eyes

Caution:

- Contents are under pressure
- Protect from direct sunlight and do not store at temperatures above 120F/50C
- After use, do not puncture or incinerate container
- Spray only in a well ventilated area
- Do not spray in presence of open flame or spark or while smoking

Stop use and ask a doctor if

- irritation occurs or if there is no improvement within 4 weeks

PREGNANCY OR BREAST FEEDING

If pregnant or breast-feeding, ask a health professional before use.

Keep out of reach of children to avoid accidental poisoning. In case of accidental ingestion, contact a doctor or Poison Control Center immediately.

Directions

- Clean the affected area and dry thoroughly
- Hold can upright
- Shake can well before each use
- Spray a thin layer of the product over the affected area twice daily (morning and night) or as directed by a doctor.
- Supervise children in the use of this product
- For athlete’s foot and ringworm, use daily for 4 weeks
- If condition persists longer, consult a doctor

Other information

- For athlete’s foot Pay special attention to spaces between the toes; wear well-fitting, ventilated shoes, and change shoes and socks at least once daily.
- This product is not effective on the scalp

INACTIVE INGREDIENT

Inactive Ingredients Butane, Panthenol, Propylene Glycol, (and) Persea Gratissima (Avocado) Fruit Extract, SD Alcohol 40-B, Undecylenamide DEA

Package label